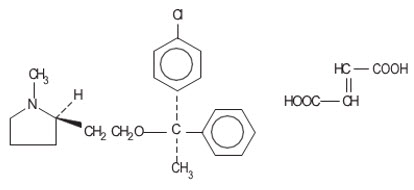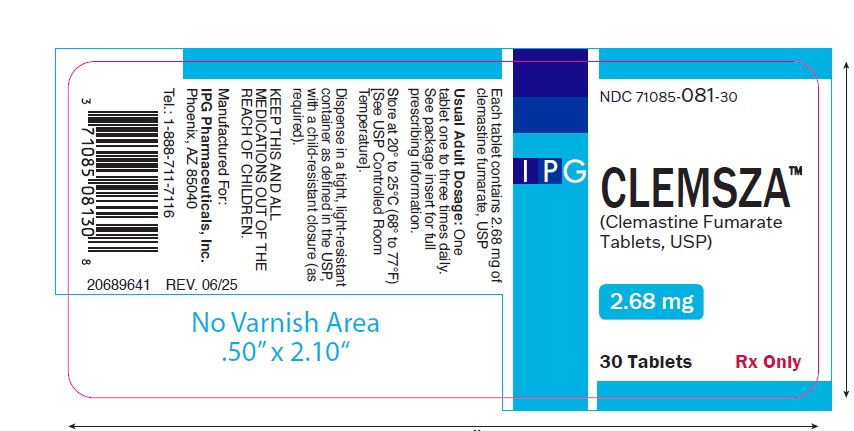 DRUG LABEL: CLEMSZA
NDC: 71085-081 | Form: TABLET
Manufacturer: IPG Pharmaceuticals, Inc.
Category: prescription | Type: HUMAN PRESCRIPTION DRUG LABEL
Date: 20250730

ACTIVE INGREDIENTS: CLEMASTINE FUMARATE 2.68 mg/1 1
INACTIVE INGREDIENTS: SILICON DIOXIDE; STARCH, CORN; LACTOSE, UNSPECIFIED FORM; POVIDONE K30; STEARIC ACID

CLEMASTINE FUMARATE TABLETS, USP

Rx only

DESCRIPTION

Clemastine belongs to the benzhydryl ether group of antihistaminic compounds. The chemical name is (+)-(2R)-2-[2-[[(R)-p-Chloro-α-methyl-α-phenylbenzyl]-oxy]ethyl]-1-methylpyrrolidine fumarate (1:1).

C21H26C1NO∙C4H4O4

M.W. 459.97

Each tablet for oral administration contains 2.68 mg of clemastine fumarate, USP. Inactive ingredients: colloidal silicon dioxide, corn starch, lactose monohydrate, povidone, pregelatinized starch and stearic acid.

CLINICAL PHARMACOLOGY

Clemastine fumarate is an antihistamine with anticholinergic (drying) and sedative side effects. Antihistamines appear to compete with histamine for cell receptor sites on effector cells. The inherently long duration of antihistaminic effects of clemastine fumarate has been demonstrated in wheal and flare studies. In normal human subjects who received histamine injections over a 24-hour period, the antihistaminic activity of clemastine reached a peak at 5 to 7 hours, persisted for 10 to 12 hours and, in some cases, for as long as 24 hours. Pharmacokinetic studies in man utilizing^3H and^14C labeled compound demonstrates that: clemastine is rapidly and nearly completely absorbed from the gastrointestinal tract, peak plasma concentrations are attained in 2 to 4 hours, and urinary excretion is the major mode of elimination.

INDICATIONS AND USAGE

Clemastine Fumarate Tablets USP, 2.68 mg are indicated for the relief of symptoms associated with allergic rhinitis such as sneezing, rhinorrhea, pruritus, and lacrimation. Clemastine Fumarate Tablets USP, 2.68 mg are also indicated for the relief of mild, uncomplicated allergic skin manifestations of urticaria and angioedema. It should be noted that clemastine fumarate is indicated for the dermatologic indications at the 2.68 mg dosage level only.

CONTRAINDICATIONS

Usage in Nursing Mothers

Because of the higher risk of antihistamines for infants generally and for newborns and prematures in particular, antihistamine therapy is contraindicated in nursing mothers.

Usage in Lower Respiratory Disease

Antihistamines should not be used to treat lower respiratory tract symptoms including asthma. Antihistamines are also contraindicated in the following conditions: Hypersensitivity to clemastine fumarate or other antihistamines of similar chemical structure. Monoamine oxidase inhibitor therapy (see Drug Interactions section).

WARNINGS

Antihistamines should be used with considerable caution in patients with: narrow angle glaucoma, stenosing peptic ulcer, pyloroduodenal obstruction, symptomatic prostatic hypertrophy, and bladder neck obstruction.

Usage in Children

Safety and efficacy of clemastine fumarate have not been established in children under the age of 12 years.

Usage in Pregnancy

Experience with this drug in pregnant women is inadequate to determine whether there is exists a potential for harm to the developing fetus.

Usage with CNS Depressants

Clemastine has additive effects with alcohol and other CNS depressants (hypnotics, sedatives, tranquilizers, etc.).

Usage in Activities Requiring Mental Alertness

Patients should be warned about engaging in activities requiring mental alertness such as driving a car or operating appliances, machinery, etc.

Usage in the Elderly (approximately 60 years or older)

Antihistamines are more likely to cause dizziness, sedation, and hypotension in elderly patients.

PRECAUTIONS

Clemastine fumarate should be used with caution in patients with: history of bronchial asthma, increased intraocular pressure, hyperthyroidism, cardiovascular disease, and hypotension.

Drug Interactions

MAO inhibitors prolong and intensify the anticholinergic (drying) effects of antihistamines.

ADVERSE REACTIONS

Transient drowsiness, the most common adverse reaction associated with clemastine fumarate, occurs relatively frequently and may require discontinuation of therapy in some instances.

Antihistaminic Compounds

It should be noted that the following reactions have occurred with one or more antihistamines and, therefore, should be kept in mind when prescribing drugs belonging to this class, including clemastine. The most frequent adverse reactions are italicized.

1. General:Urticaria, drug rash, anaphylactic shock, photosensitivity, excessive perspiration, chills, dryness of the mouth, nose, and throat.
2. Cardiovascular System:Hypotension, headache, palpitations, tachycardia, extrasystoles.
3. Hematologic System:Hemolytic anemia, thrombocytopenia, agranulocytosis.
4. Nervous System: Sedation, sleepiness, dizziness, disturbed coordination, fatigue, confusion, restlessness, excitation, nervousness, tremor, irritability, insomnia, euphoria, paresthesias, blurred vision, diplopia, vertigo, tinnitus, acute labyrinthitis, hysteria, neuritis, convulsions.
5. GI System:Epigastric distress, anorexia, nausea, vomiting, diarrhea, constipation.
6. GU System:Urinary frequency, difficult urination, urinary retention, early menses.
7. Respiratory System:Thickening of bronchial secretions, tightness of chest and wheezing, nasal stuffiness.

OVERDOSAGE

Antihistamine overdosage reactions may vary from central nervous system depression to stimulation.

Stimulation is particularly likely in children. Atropine-like signs and symptoms: dry mouth; fixed, dilated pupils; flushing; and gastrointestinal symptoms may also occur.

If vomiting has not occurred spontaneouslythe conscious patient should be induced to vomit. This is best done by having him drink a glass of water or milk after which he should be made to gag. Precautions against aspiration must be taken, especially in infants and children. If vomiting is unsuccessful gastric lavage is indicated within 3 hours after ingestion and even later if large amounts of milk or cream were given beforehand. Isotonic and 1/2 isotonic saline is the lavage solution of choice.

Saline cathartics, such as milk of magnesia, by osmosis draw water into the bowel and therefore, are valuable for their action in rapid dilution of bowel content.

Stimulantsshould notbe used.

Vasopressors may be used to treat hypotension.

DOSAGE AND ADMINISTRATION

DOSAGE SHOULD BE INDIVIDUALIZED ACCORDING TO THE NEEDS AND RESPONSE OF THE PATIENT.

Clemastine Fumarate Tablets 2.68 mg

The maximum recommended dosage is one tablet three times daily. Many patients respond favorably to a single dose which may be repeated as required, but not to exceed three tablets daily.

HOW SUPPLIED

Clemastine Fumarate Tablets USP, 2.68 mg are white, round, scored tablets debossed with "NH" and "268". Tablets are packaged in bottles of 30 (NDC 71085-081-30)

STORAGE AND HANDLING

Store at 20° to 25°C (68° to 77°F) [See USP Controlled Room Temperature]. Dispense in a tight, light-resistant container as defined in the USP, with a child-resistant closure (as required).

Manufactured For:
IPG Pharmaceuticals, Inc.
Phoenix, AZ 85040
Tel.: 1-888-711-7116

Rev. 06/2025